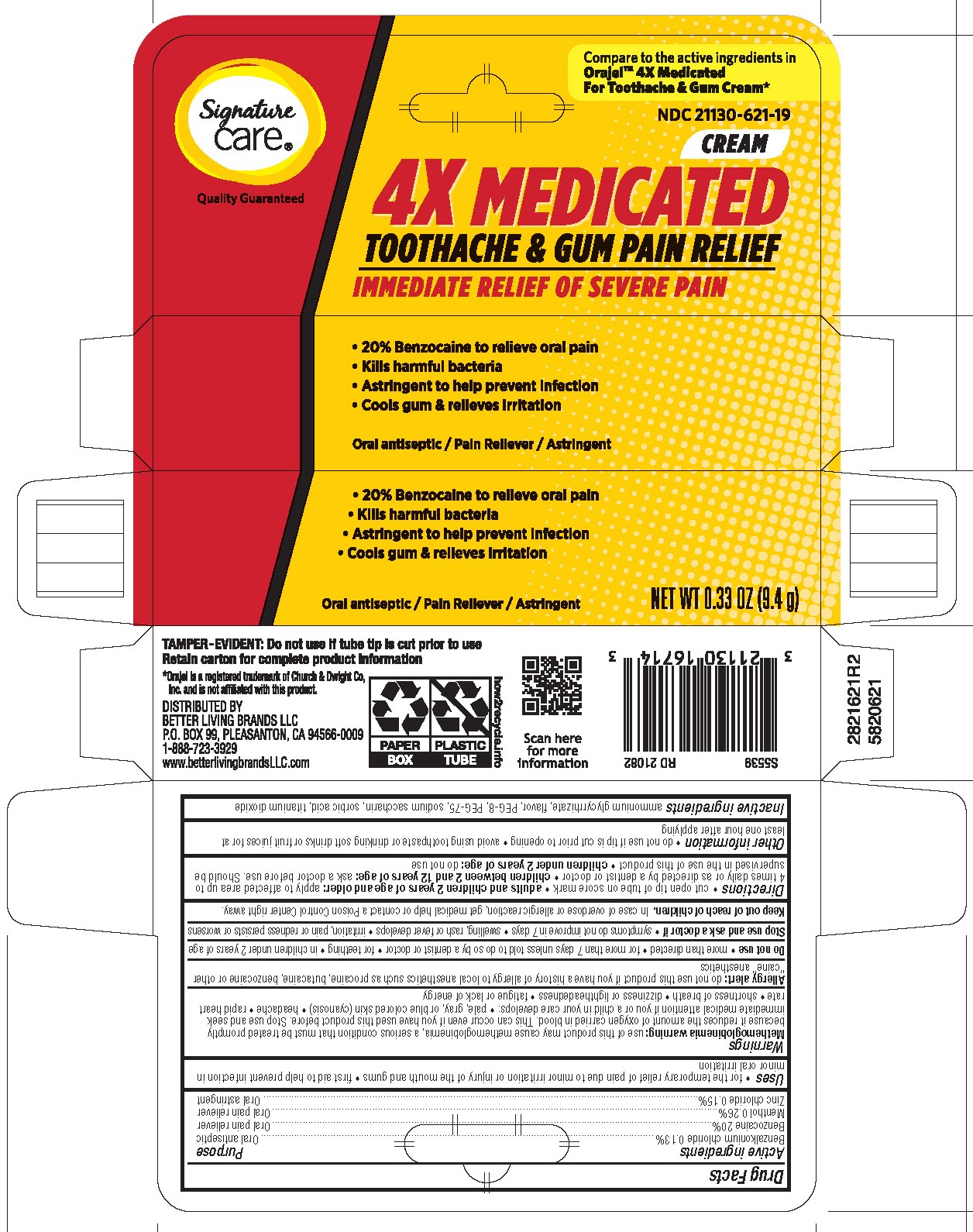 DRUG LABEL: 4x Medicated Gum Cream
NDC: 21130-621 | Form: CREAM
Manufacturer: Albertsons
Category: otc | Type: HUMAN OTC DRUG LABEL
Date: 20251121

ACTIVE INGREDIENTS: BENZALKONIUM CHLORIDE 0.13 g/100 g; MENTHOL, UNSPECIFIED FORM 0.25 g/100 g; BENZOCAINE 20 g/100 g; ZINC CHLORIDE 0.15 g/100 g
INACTIVE INGREDIENTS: AMMONIUM GLYCYRRHIZATE; TITANIUM DIOXIDE; SORBIC ACID; POLYETHYLENE GLYCOL 400; SACCHARIN SODIUM; POLYETHYLENE GLYCOL 3350

5820621 Albertsons 4x Cream

ACTIVE INGREDIENT

Benzalkonium chloride 0.13%

Benzocaine 20%

Menthol 0.26%

Zinc chloride 0.15%

PURPOSE

Oral antiseptic

Oral pain reliever

Oral pain reliever

Oral astringent

INDICATIONS AND USAGE

- for the temporary relief of pain due to minor irritation or injury of the mouth and gums
- first aid to help prevent infection in minor oral irritation

DOSAGE AND ADMINISTRATION

- cut open tip of tube on score mark
- adults and children 2 years of age and older: apply to affected area up to 4 times daily or as directed by a dentist or doctor
- children between 2 and 12 years of age: ask a doctor before use. Should be supervised in the use of this product
- children under 2 years of age: do not use

WARNINGS

Methemoglobinemia warning: use of this product may cause methemoglobinemia, a serious condition that must be treated promptly because it reduces the amount of oxygen carried in blood. This can occur even if you have used this product before. Stop use and seek immediate medical attention if you or a child in your care develops:

- pale, gray, or blue colored skin (cyanosis)
- headache
- rapid heart rate
- shortness of breath
- dizziness or lightheadedness
- fatigue or lack of energy

Allergy alert: do not use this product if you have a history of allergy to local anesthetics such as procaine, butacaine, benzocaine or other "caine" anesthetics

Do not use * more than directed * for more than 7 days unless told to do so by a dentist or doctor * for teething * in children under 2 years of age

Stop use and ask a doctor if * swelling, rash or fever develops * irritation, pain or redness persists or worsens * symptoms do not improve in 7 days * allergic reaction occurs

Keep out of reach of children. In case of overdose or allergic reaction, get medical help or contact a Poison Control Center right away.

- do not use if tip is cut prior to opening
- avoid using toothpaste or drinking soft drinks or fruit juices for at least one hour after applying

INACTIVE INGREDIENT

ammonium glycyrrhizate, flavor, PEG-8, PEG-75, sodium saccharin, sorbic acid, titanium dioxide